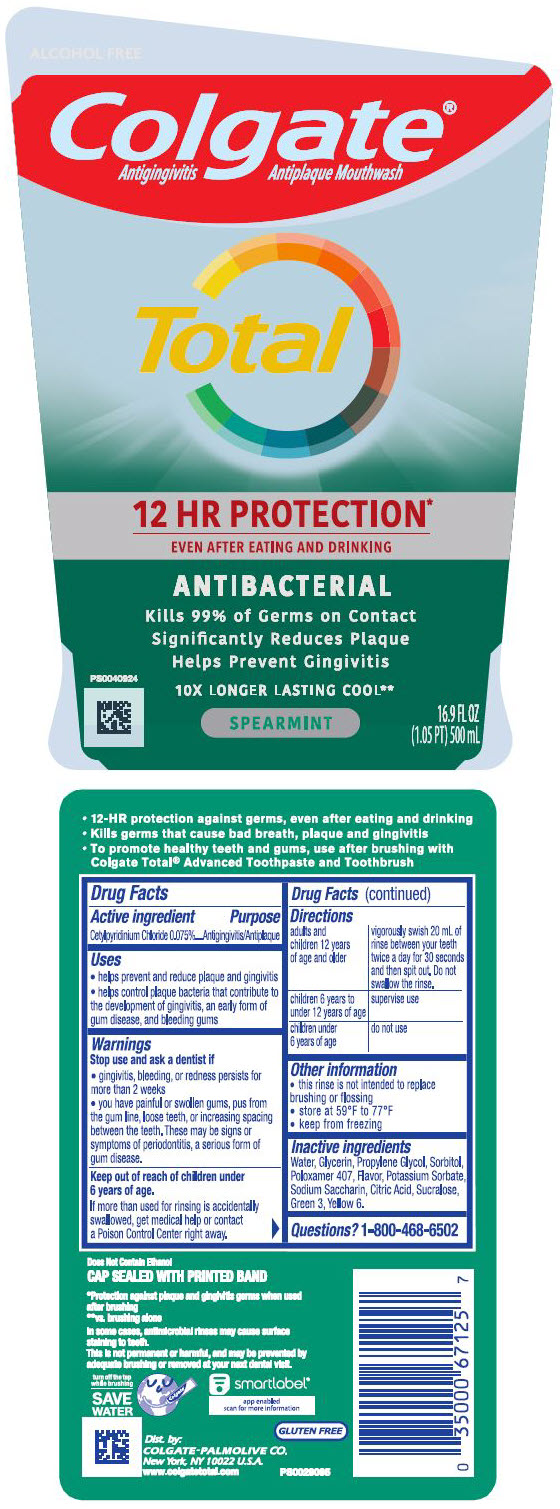 DRUG LABEL: Colgate Total 12 Hr Pro-Shield  Spearmint Surge
NDC: 35000-731 | Form: RINSE
Manufacturer: Colgate-Palmolive Company
Category: otc | Type: HUMAN OTC DRUG LABEL
Date: 20250219

ACTIVE INGREDIENTS: CETYLPYRIDINIUM CHLORIDE 15 mg/20 mL
INACTIVE INGREDIENTS: WATER; GLYCERIN; PROPYLENE GLYCOL; SORBITOL; POLOXAMER 407; POTASSIUM SORBATE; SACCHARIN SODIUM; ANHYDROUS CITRIC ACID; SUCRALOSE; FD&C GREEN NO. 3; FD&C YELLOW NO. 6

Colgate® Total™ 12 Hr Pro-Shield Spearmint Surge

Drug Facts

Active ingredient

Cetylpyridinium chloride 0.075%

Purpose

Antigingivitis/Antiplaque

Uses

- helps prevent and reduce plaque and gingivitis
- helps control plaque bacteria that contribute to the development of gingivitis, an early form of gum disease, and bleeding gums

Warnings

Stop use and ask a dentist if

- gingivitis, bleeding, or redness persists for more than 2 weeks
- you have painful or swollen gums, pus from the gum line, loose teeth, or increasing spacing between the teeth. These may be signs or symptoms of periodontitis, a serious form of gum disease.

Keep out of reach of children under 6 years of age.

If more than used for rinsing is accidentally swallowed, get medical help or contact a Poison Control Center right away.

Directions

adults and children 12 years of age and older | vigorously swish 20 mL of rinse between your teeth twice a day for 30 seconds and then spit out. Do not swallow the rinse.
children 6 years to under 12 years of age | supervise use
children under 6 years of age | do not use

Other information

- this rinse is not intended to replace brushing or flossing
- store at 59°F to 77°F
- keep from freezing

Inactive ingredients

water, glycerin, propylene glycol, sorbitol, poloxamer 407, flavor, potassium sorbate, sodium saccharin, citric acid, sucralose, FD&C green no. 3, FD&C yellow no. 6

Questions?

1-800-468-6502

Dist. by:
COLGATE-PALMOLIVE CO.
New York, NY 10022 U.S.A.

PRINCIPAL DISPLAY PANEL - 500 mL Bottle Label

ALCOHOL FREE

Colgate®
Antigingivitis Antiplaque Mouthwash

Total

12 HR PROTECTION*
EVEN AFTER EATING AND DRINKING

ANTIBACTERIAL

Kills 99% of Germs on Contact
Significantly Reduces Plaque
Helps Prevent Gingivitis

10X LONGER LASTING COOL**

SPEARMINT

P80040924

16.9 FL OZ
(1.05 PT) 500 mL